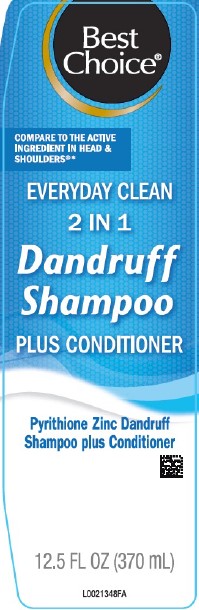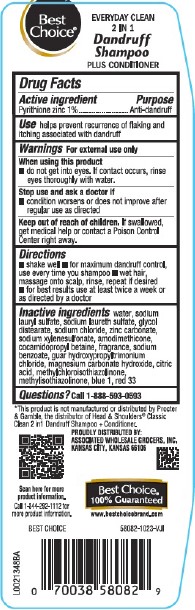 DRUG LABEL: Dandruff
NDC: 63941-311 | Form: SHAMPOO
Manufacturer: Valu Merchandisers Company
Category: otc | Type: HUMAN OTC DRUG LABEL
Date: 20260216

ACTIVE INGREDIENTS: PYRITHIONE ZINC 10 mg/1 mL
INACTIVE INGREDIENTS: WATER; SODIUM LAURYL SULFATE; SODIUM LAURETH SULFATE; GLYCOL DISTEARATE; SODIUM CHLORIDE; ZINC CARBONATE; SODIUM XYLENESULFONATE; AMODIMETHICONE (800 CST); COCAMIDOPROPYL BETAINE; SODIUM BENZOATE; GUAR HYDROXYPROPYLTRIMONIUM CHLORIDE (1.7 SUBSTITUENTS PER SACCHARIDE); MAGNESIUM CARBONATE HYDROXIDE; CITRIC ACID MONOHYDRATE; METHYLCHLOROISOTHIAZOLINONE; METHYLISOTHIAZOLINONE; FD&C BLUE NO. 1; D&C RED NO. 33

Best Choice 311.007/311AN
Dandruff Shampoo, Everyday Clean 2 in 1

Claims

Best Choice®

Everyday Clean

2 in 1

Dandruff Shampoo

PLUS CONDITIONER

Active ingredient

Pyrithione zinc 1%

Purpose

Anti-dandruff

Use

helps prevent recurrence of flaking and itching associated with dandruff

Warnings

For external use only

When using this product

- do not get into eyes. If contact occurs, rinse eyes thoroughly with water.

Stop use and ask a doctor if

- condition worsens or does not improve after regular use as directed

Keep out of reach of children.

If swallowed, get medical help or contact a Poison Control Center right away.

Directions

- shake well
- for maximum dandruff control, use every time you shampoo
- wet hair, massage onto scalp, rinse, repeat if desired
- for best results use at least twice a week or as directed by a doctor

Inactive ingredients

water, sodium lauryl sulfate, sodium laureth sulfate, glycol distearate, sodium chloride, zinc carbonate, sodium xylenesulfonate, amodimethicone, cocamidopropyl betaine, fragrance, sodium benzoate, guar hydroxypropyltrimonium chloride, magnesium carbonate hydroxide, citric acid, methylchloroisothiazolinone, methylisothiazolinone, blue 1, red 33

Questions?

Call 1-888-593-0593

Disclaimer

*This product is not manufactured or distributed by Procter & Gamble, the distributor of Head & Shoulders® Classic Clean 2 in 1 Dandruff Shampoo & Conditioner.

Adverse Reactions

PROUDLY DISTRIBUTED BY:

ASSOCIATED WHOLESALE GROCERS, INC.

KANSAS CITY, KA 66106

Scan here for more information.

Call1-844-292-1112 for more product information.

Best Choice

100% Guaranteed

www.bestchoicebrand.com

Principal panel display

Best Choice®

COMPARE TO THE ACTIVE INGREDIENT IN HEAD & SHOULDERS®*

EVERYDAY CLEAN

2 IN 1

Dandruff Shampoo

PLUS CONDITIONER

Pyrithione Zinc Dandruff Shampoo plus Conditioner

12.5 FL OZ (370 mL)